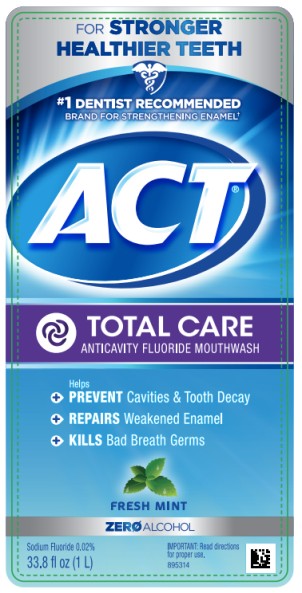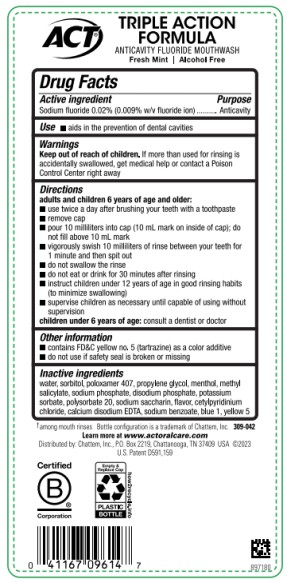 DRUG LABEL: Act Total Care Anticavity Fluoride Fresh Mint
NDC: 41167-0943 | Form: RINSE
Manufacturer: Chattem, Inc.
Category: otc | Type: HUMAN OTC DRUG LABEL
Date: 20250722

ACTIVE INGREDIENTS: SODIUM FLUORIDE 0.09 mg/1 mL
INACTIVE INGREDIENTS: EDETATE CALCIUM DISODIUM; CETYLPYRIDINIUM CHLORIDE; SODIUM PHOSPHATE, DIBASIC, DIHYDRATE; FD&C GREEN NO. 3; MENTHOL; METHYL SALICYLATE; POLOXAMER 407; POLYSORBATE 20; POTASSIUM SORBATE; PROPYLENE GLYCOL; SODIUM BENZOATE; SODIUM PHOSPHATE; SACCHARIN SODIUM ANHYDROUS; SORBITOL; WATER; FD&C YELLOW NO. 5; FD&C BLUE NO. 1

Act Total Care Anticavity Fluoride Rinse Fresh Mint

Drug Facts

Active ingredient

Sodium fluoride 0.02% (0.009% w/v fluoride ion)

Purpose

Anticavity

Use

- aids in the prevention of dental cavities

Warnings

Keep out of reach of children.

If more than used for rinsing is accidentally swallowed, get medical help or contact a Poison Control Center right away.

Directions

adults and children 6 years of age and older:

- use twice a day after brushing your teeth with a toothpaste
- remove cap
- pour 10 milliliters (10 mL mark on inside of cap); do not fill above 10 mL mark
- vigorously swish 10 milliliters of rinse between your teeth for 1 minute and then spit out
- do not swallow the rinse
- do not eat or drink for 30 minutes after rinsing
- instruct children under 12 years of age in good rinsing habits (to minimize swallowing)
- supervise children as necessary until capable of using without supervision

children under 6 years of age: consult a dentist or doctor

Other information

- contains FD&C yellow no. 5 (tartrazine) as a color additive
- do not use if safety seal is broken or missing

Inactive ingredients

water, sorbitol, poloxamer 407, propylene glycol, menthol, methyl salicylate, sodium phosphate, disodium phosphate, potassium sorbate, polysorbate 20, sodium saccharin, flavor, cetylpyridinium chloride, calcium disodium EDTA, sodium benzoate, blue 1, yellow 5

Learn more at www. ACTFLUORIDE.com

PRINCIPAL DISPLAY PANEL

#1 DENTIST RECOMMENDED
FLUORIDE BRAND
ACT
Anticavity
Fluoride Mouthwash
alcohol free
FRESH MINT
33.8 fl oz (1 L)